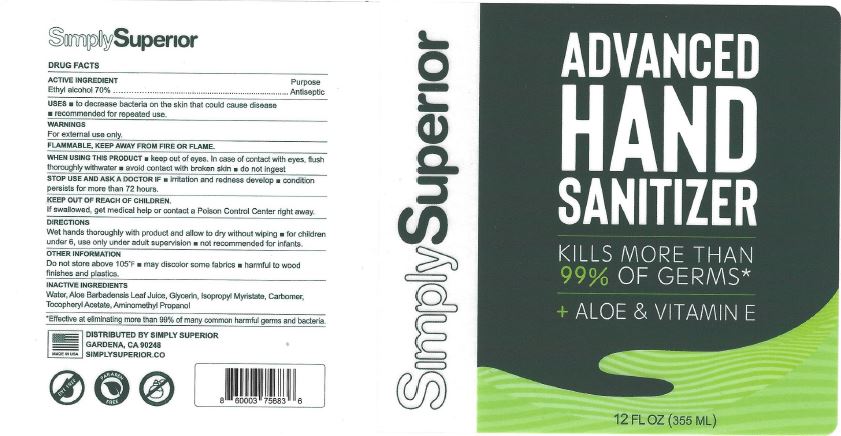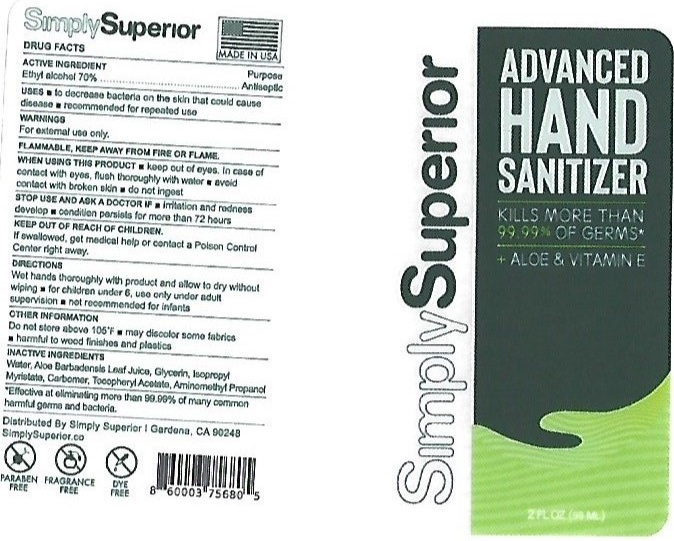 DRUG LABEL: ADVANCED HAND SANITIZER

NDC: 50518-308 | Form: GEL
Manufacturer: CUSTOM RESEARCH LABS INC
Category: otc | Type: HUMAN OTC DRUG LABEL
Date: 20220329

ACTIVE INGREDIENTS: ALCOHOL 70 mL/100 mL
INACTIVE INGREDIENTS: WATER; ALOE VERA LEAF; GLYCERIN; ISOPROPYL MYRISTATE; CARBOMER HOMOPOLYMER, UNSPECIFIED TYPE; .ALPHA.-TOCOPHEROL ACETATE; AMINOMETHYLPROPANOL

CRL (as CMO) - SIMPLY SUPERIOR - ADVANCED HAND SANITIZER - 70% ETHYL ALCOHOL (50518-308)

ACTIVE INGREDIENT

ETHYL ALCOHOL 70%

PURPOSE

ANTISEPTIC

USES

- TO DECREASE BACTERIA ON THE SKIN THAT COULD CAUSE DISEASE
- RECOMMENDED FOR REPEATED USE

WARNINGS

FOR EXTERNAL USE ONLY.

FLAMMABLE, KEEP AWAY FROM FIRE OR FLAME.

WHEN USING THIS PRODUCT

- KEEP OUT OF EYES. IN CASE OF CONTACT WITH EYES, FLUSH THOROUGHLY WITH WATER.
- AVOID CONTACT WITH BROKEN SKIN
- DO NOT INHALE OR INGEST

STOP USE AND ASK A DOCTOR IF

- IRRITATION AND REDNESS DEVELOP
- CONDITION PERSISTS FOR MORE THAN 72 HOURS

KEEP OUT OF REACH OF CHILDREN.

IF SWALLOWED, GET MEDICAL HELP OR CONTACT A POISON CONTROL CENTER RIGHT AWAY.

DIRECTIONS

WET HANDS THOROUGHLY WITH PRODUCT AND ALLOW TO DRY WITHOUT WIPING

- FOR CHILDREN UNDER 6, USE ONLY UNDER ADULT SUPERVISION
- NOT RECOMMENDED FOR INFANTS

OTHER INFORMATION

DO NOT STORE ABOVE 105°F

- MAY DISCOLOR SOME FABRICS
- HARMFUL TO WOOD FINISHES AND PLASTICS

INACTIVE INGREDIENTS

WATER, ALOE BARBADENSIS LEAF JUICE, GLYCERIN, ISOPROPYL MYRISTATE, CARBOMER, TOCOPHERYL ACETATE, AMINOMETHYL PROPANOL